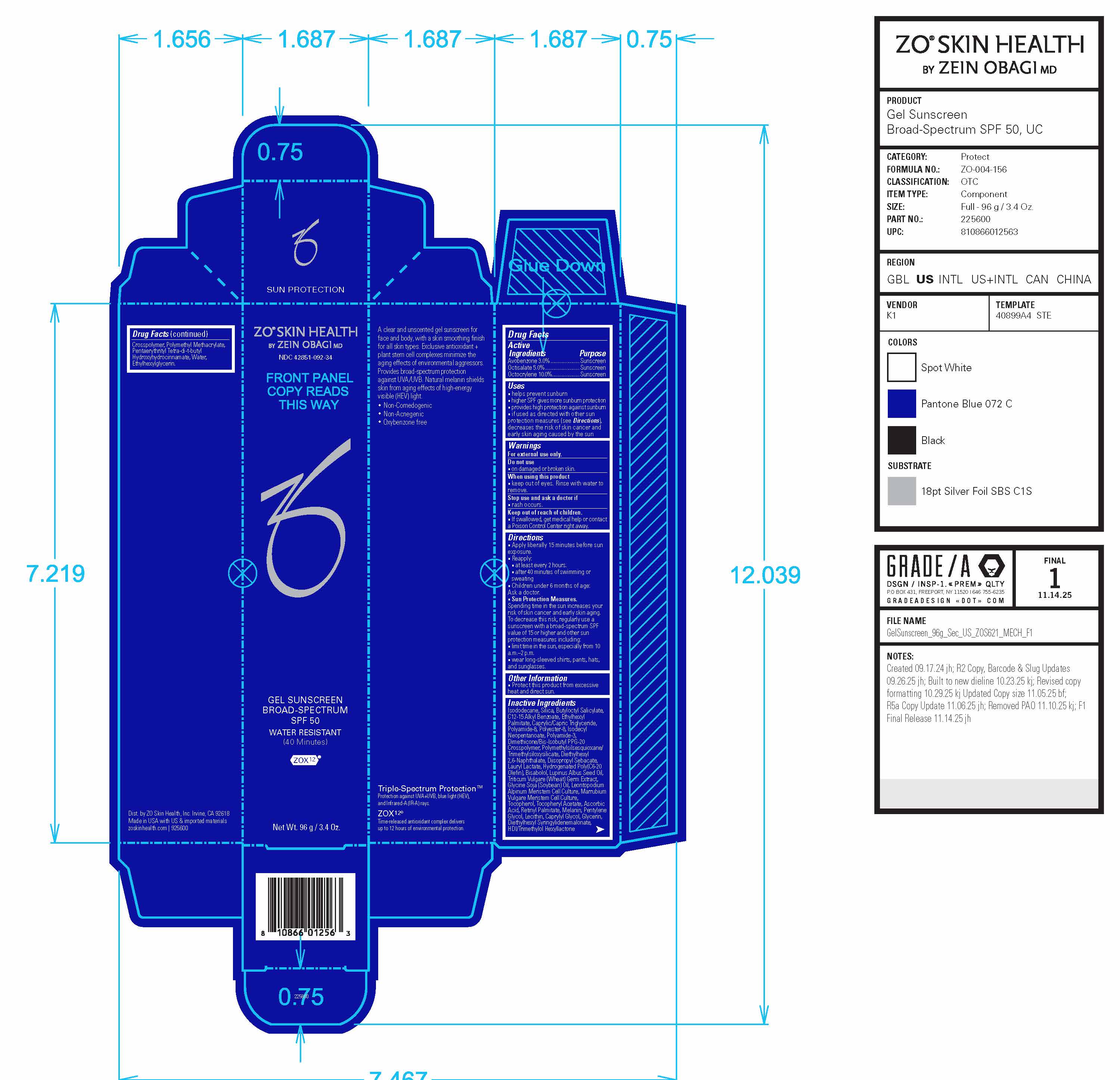 DRUG LABEL: ZO Skin Health Gel Sunscreen Broad-Spectrum SPF 50
NDC: 42851-092 | Form: GEL
Manufacturer: ZO Skin Health, Inc.
Category: otc | Type: HUMAN OTC DRUG LABEL
Date: 20251126

ACTIVE INGREDIENTS: OCTOCRYLENE 4.5 g/45 g; AVOBENZONE 1.35 g/45 g; OCTISALATE 2.25 g/45 g
INACTIVE INGREDIENTS: SILICON DIOXIDE; ALKYL (C12-15) BENZOATE; ETHYLHEXYL PALMITATE; ISODODECANE; POLYAMIDE-8 (4500 MW); POLYESTER-8 (1400 MW, CYANODIPHENYLPROPENOYL CAPPED); DIISOPROPYL SEBACATE; HEXAMETHYLENE DIISOCYANATE/TRIMETHYLOL HEXYLLACTONE CROSSPOLYMER; PENTAERYTHRITOL TETRAKIS(3-(3,5-DI-TERT-BUTYL-4-HYDROXYPHENYL)PROPIONATE); WATER; DIETHYLHEXYL SYRINGYLIDENEMALONATE; TOCOPHEROL; DIMETHICONE/BIS-ISOBUTYL PPG-20 CROSSPOLYMER; WHEAT GERM; LECITHIN, SOYBEAN; GLYCERIN; DIETHYLHEXYL 2,6-NAPHTHALATE; POLYAMIDE-3 (12000 MW); BUTYLOCTYL SALICYLATE; MEDIUM-CHAIN TRIGLYCERIDES; POLY(METHYL METHACRYLATE; 450000 MW); ETHYLHEXYLGLYCERIN; ISODECYL NEOPENTANOATE; POLYMETHYLSILSESQUIOXANE/TRIMETHYLSILOXYSILICATE; LAURYL LACTATE; CAPRYLYL GLYCOL; PENTYLENE GLYCOL; LUPINUS ALBUS SEED OIL; SOYBEAN OIL; ALPHA-TOCOPHEROL ACETATE; HYDROGENATED C6-20 POLYOLEFIN (100 CST); LEVOMENOL; ASCORBIC ACID; VITAMIN A PALMITATE

ZO® Skin Health Gel Sunscreen Broad-Spectrum SPF 50
National Drug Code 42851-092-34
Formula No. ZO-004-156

Drug Facts

Active Ingredients

Active Ingredients | Purpose
Avobenzone 3.0%......... | Sunscreen
Octisalate 5.0%............ | Sunscreen
Octocrylene 10.0% | Sunscreen

Uses

- helps prevent sunburn
- higher SPF gives more sunburn protection
- provides high protection against sunburn
- if used as directed with other sun protection measures (see Directions), decreases the risk of skin cancer and early skin aging caused by the sun

Warnings

For external use only.

Do not use

- on damaged or broken skin.

When using this product

- keep out of eyes. Rinse with water to remove.

Stop use and ask a doctor if

- rash occurs.

Keep out of reach of children.

- If swallowed, get medical help or contact a Poison Control Center right away.

Directions

- Apply liberally 15 minutes before sun exposure.
- Reapply: ■ at least every 2 hours. ■ after 40 minutes of swimming or sweating
- Children under 6 months of age: Ask a doctor.
- Sun Protection Measures. Spending time in the sun increases your risk of skin cancer and early skin aging. To decrease this risk, regularly use a sunscreen with a broad-spectrum SPF value of 15 or higher and other sun protection measures including: ■ limit time in the sun, especially from 10 a.m.–2 p.m. ■ wear long-sleeved shirts, pants, hats, and sunglasses.

Other Information

Protect this product from excessive heat and direct sun.

Inactive Ingredients

Isododecane, Silica, Butyloctyl Salicylate, C12-15 Alkyl Benzoate, Ethylhexyl Palmitate, Caprylic/Capric Triglyceride, Polyamide-8, Polyester-8, Isodecyl Neopentanoate, Polyamide-3, Dimethicone/Bis-Isobutyl PPG-20 Crosspolymer, Polymethylsilsesquioxane/Trimethylsiloxysilicate, Diethylhexyl 2,6-Naphthalate, Diisopropyl Sebacate, Lauryl Lactate, Hydrogenated Poly(C6-20 Olefin), Bisabolol, Lupinus Albus Seed Oil, Triticum Vulgare (Wheat) Germ Extract, Glycine Soja (Soybean) Oil, Leontopodium Alpinum Meristem Cell Culture, Marrubium Vulgare Meristem Cell Culture, Tocopherol, Tocopheryl Acetate, Ascorbic Acid, Retinyl Palmitate, Melanin, Pentylene Glycol, Lecithin, Caprylyl Glycol, Glycerin, Diethylhexyl Syringylidenemalonate, HDI/Trimethylol Hexyllactone Crosspolymer, Polymethyl Methacrylate, Pentaerythrityl Tetra-di-t-butyl Hydroxyhydrocinnamate, Water, Ethylhexylglycerin

Principal Display Panel

ZO® Skin Health Gel Sunscreen Broad-Spectrum SPF 50

Water-Resistant

(40 Minutes)

ZOX12®

Triple-Spectrum Protection™
Protection against UVA+UVB, blue light (HEV),
and Infrared-A (IR-A) rays.
ZOX12®
Time-released antioxidant complex delivers
up to 12 hours of environmental protection.

Dist. by ZO Skin Health, Inc. Irvine, CA 92618

Made in USA with US & imported materials

zoskinhealth.com